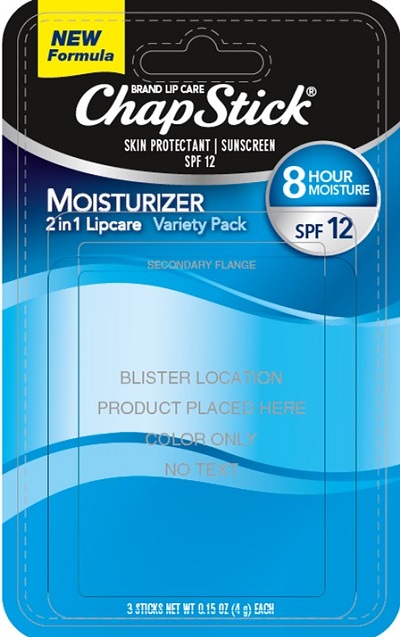 DRUG LABEL: Chapstick Moisturizer Variety Pack
NDC: 0573-1959 | Form: KIT | Route: TOPICAL
Manufacturer: Haleon US Holdings LLC
Category: otc | Type: HUMAN OTC DRUG LABEL
Date: 20240412

ACTIVE INGREDIENTS: AVOBENZONE 30 mg/1 g; HOMOSALATE 40 mg/1 g; OCTISALATE 45 mg/1 g; OCTOCRYLENE 26 mg/1 g; PETROLATUM 384 mg/1 g; AVOBENZONE 30 mg/1 g; HOMOSALATE 40 mg/1 g; OCTISALATE 45 mg/1 g; OCTOCRYLENE 26 mg/1 g; PETROLATUM 369 mg/1 g; AVOBENZONE 30 mg/1 g; HOMOSALATE 40 mg/1 g; OCTISALATE 45 mg/1 g; OCTOCRYLENE 26 mg/1 g; PETROLATUM 384 mg/1 g
INACTIVE INGREDIENTS: ALOE VERA LEAF; ISOMETHYL-.ALPHA.-IONONE; ANISYL ALCOHOL; BENZYL ALCOHOL; BENZYL BENZOATE; BENZYL SALICYLATE; BUTYLATED HYDROXYTOLUENE; CETYL ALCOHOL; CARNAUBA WAX; ISOCETYL STEARATE; LANOLIN; MINERAL OIL; MYRISTYL ALCOHOL; PARAFFIN; STEARYL ALCOHOL; TOCOPHEROL; .ALPHA.-TOCOPHEROL ACETATE; WHITE WAX; ALOE VERA LEAF; BENZYL ALCOHOL; BUTYLATED HYDROXYTOLUENE; CETYL ALCOHOL; CARNAUBA WAX; ISOCETYL STEARATE; LANOLIN; MINERAL OIL; MYRISTYL ALCOHOL; PARAFFIN; STEARYL ALCOHOL; TOCOPHEROL; .ALPHA.-TOCOPHEROL ACETATE; WHITE WAX; ALOE VERA LEAF; BUTYLATED HYDROXYTOLUENE; FD&C BLUE NO. 1 ALUMINUM LAKE; MEDIUM-CHAIN TRIGLYCERIDES; CETYL ALCOHOL; CARNAUBA WAX; ISOCETYL STEARATE; ISOPROPYL TITANIUM TRIISOSTEARATE; LANOLIN; MINERAL OIL; MYRISTYL ALCOHOL; PARAFFIN; D&C RED NO. 6; D&C RED NO. 7; ALUMINUM OXIDE; STEARYL ALCOHOL; SACCHARIN; SYNTHETIC WAX (1200 MW); TOCOPHEROL; .ALPHA.-TOCOPHEROL ACETATE; .ALPHA.-TOCOPHEROL LINOLEATE, D-; WHITE WAX

Drug Facts

Active ingredients (Original)

Avobenzone 3.0%

Homosalate 4.0%

Octisalate 4.5%

Octocrylene 2.6%

White Petrolatum 38.4%

Active ingredients (Cool Mint)

Avobenzone 3.0%

Homosalate 4.0%

Octisalate 4.5%

Octocrylene 2.6%

White Petrolatum 36.9%

Active ingredients (Black Cherry)

Avobenzone 3.0%

Homosalate 4.0%

Octisalate 4.5%

Octocrylene 2.6%

White Petrolatum 36.8%

Purposes

Sunscreens

Skin protectant

Uses

- helps prevent sunburn
- helps prevent and temporarily protects chafed, chapped or cracked lips
- helps prevent and protect from the drying effects of wind and cold weather

Warnings

Skin Cancer/ Skin Aging Alert:Spending time in the sun increases your risk of skin cancer and early skin aging. This product has been shown only to help prevent sunburn, not skin cancer or early skin aging.

For external use only

Do not useon damaged or broken skin

Stop use and ask a doctor ifrash occurs

WHEN USING

When using this productkeep out of eyes. Rinse with water to remove.

Keep out of reach of children.If swallowed, get medical help or contact a Poison Control Center right away.

Directions

- apply liberally 15 minutes before sun exposure
- reapply at least every 2 hours
- use a water resistant sunscreen if swimming or sweating
- children under 6 months of age: Ask a doctor

Other information

- store at 20-25°C (68-77°F)
- protect the product from excessive heat and direct sun

Inactive ingredients (Original)

aloe barbadensis leaf extract, alpha-isomethyl ionone, anise alcohol, benzyl alcohol, benzyl benzoate, benzyl salicylate, BHT, cetyl alcohol, copernicia cerifera (carnauba) wax, fragrance, isocetyl stearate, isopropyl lanolate, lanolin, mineral oil, myristyl alcohol, paraffin, stearyl alcohol, tocopherol, tocopheryl acetate, tocopheryl linoleate/oleate, white beeswax

Inactive ingredients (Cool Mint)

aloe barbadensis leaf extract, benzyl alcohol, BHT, cetyl alcohol, copernicia cerifera, (carnauba) wax, flavor, isocetyl stearate, isopropyl lanolate, lanolin, mineral oil, myristyl alcohol, paraffin, stearyl alcohol, tocopherol, tocopheryl acetate, tocopheryl linoleate/oleate, white beeswax

Inactive ingredients (Black Cherry)

aloe barbadensis leaf extract, BHT, blue 1 lake, caprylic/capric triglyceride, cetyl alcohol, copernicia cerifera (carnauba) wax, isocetyl stearate, isopropyl lanolate, isopropyl titanium triisostearate, lanolin, mineral oil, myristyl alcohol, natural flavor, paraffin, red 6 lake, red 7 lake, stearyl alcohol, synthetic wax,

tocopherol, tocopheryl acetate, tocopheryl linoleate/oleate, white beeswax

Questions?

1-800-245-1040

Additional information

Paraben Free

Moisturizer

Variety Pack

Dist by: GSK CH, Warren, NJ 07059

For most recent product information,

visit www.chapstick.com

Trademarks owned or licensed by GSK.

©2022 GSK or licensor

PRINCIPAL DISPLAY PANEL

NEW

Formula

BRAND LIP CARE
ChapStick®

SKIN PROTECTANT | SUNSCREEN
SPF 12

MOISTURIZER
2 in 1 Lipcare Variety Pack

8HOUR MOISTURE
SPF 12

3 STICKS

NET WT 0.15 OZ

(4 g) EACH

000073773